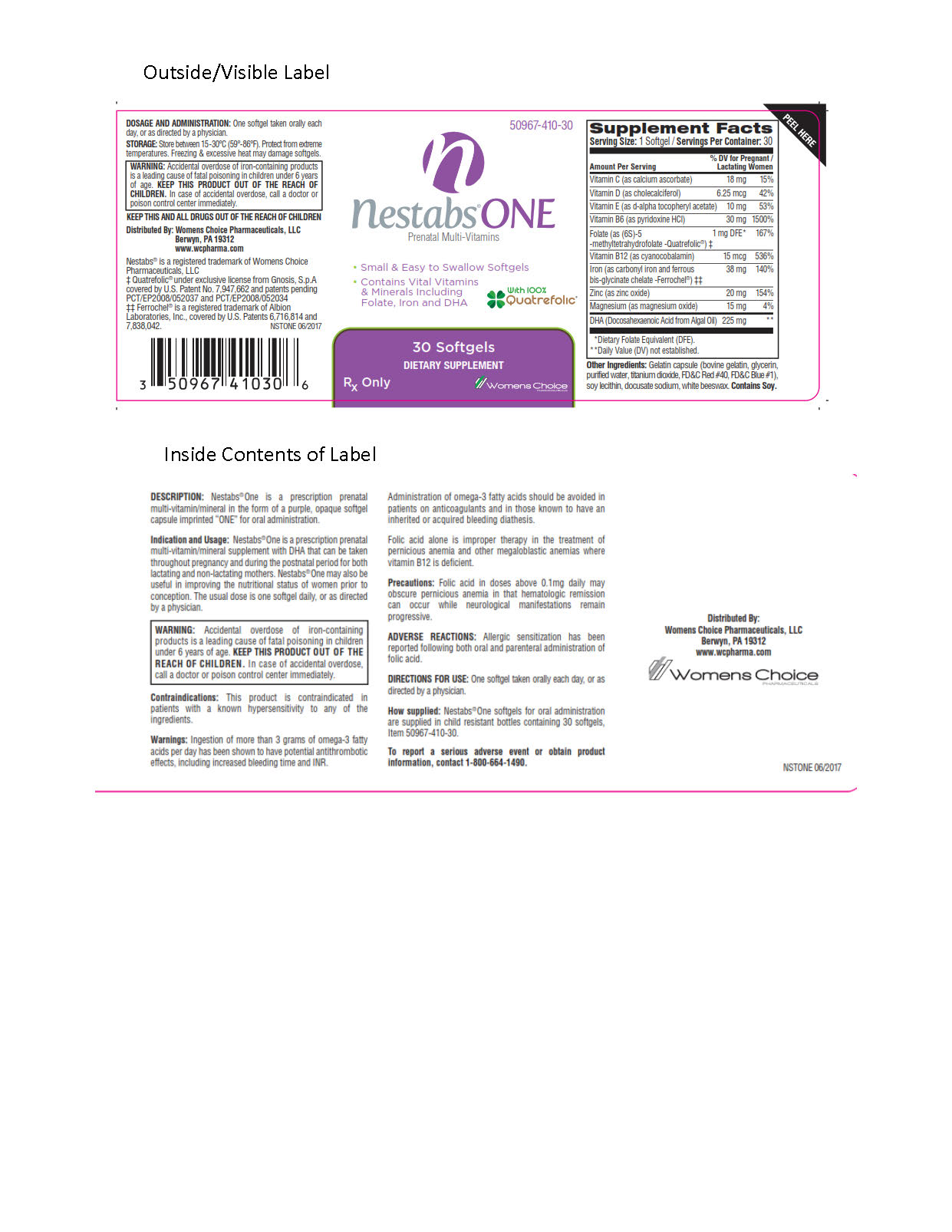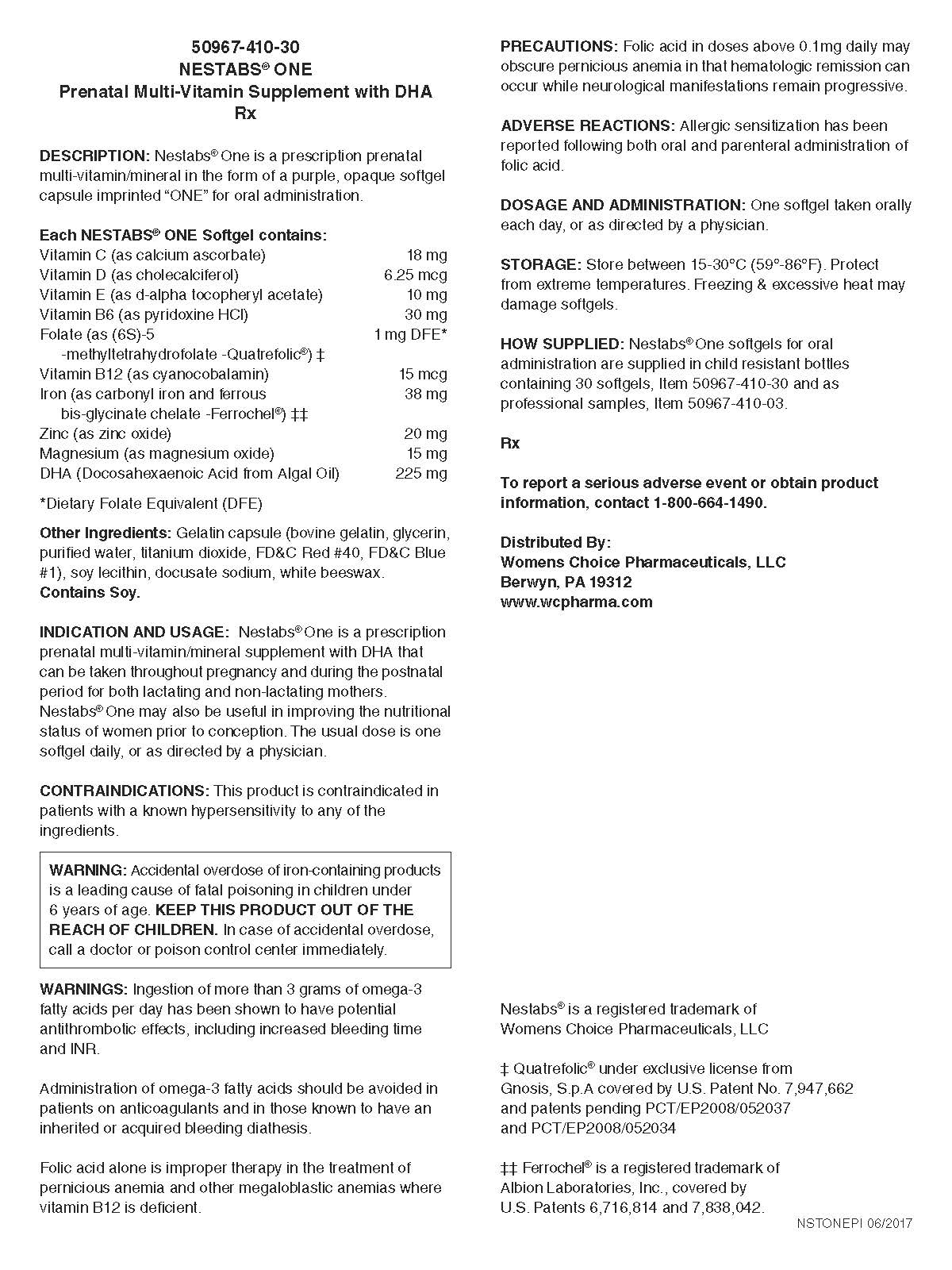 DRUG LABEL: Nestabs ONE
NDC: 50967-410 | Form: CAPSULE, GELATIN COATED
Manufacturer: Womens Choice Pharmaceuticals, LLC
Category: prescription | Type: HUMAN PRESCRIPTION DRUG LABEL
Date: 20250428

ACTIVE INGREDIENTS: ZINC OXIDE 1 mg/1 1; FOLIC ACID 1 mg/1 1; ANTAZOLINE 225 mg/1 1; TOCOPHEROL 10 mg/1 1; CALCIUM ASCORBATE 18 mg/1 1; CYANOCOBALAMIN 15 ug/1 1; MAGNESIUM OXIDE 15 mg/1 1; CHOLECALCIFEROL 6.25 ug/1 1; PYRIDOXINE HYDROCHLORIDE 30 mg/1 1; IRON 38 mg/1 1
INACTIVE INGREDIENTS: DOCUSATE SODIUM; WHITE WAX; LECITHIN, SOYBEAN; WATER; GELATIN TYPE B BOVINE (160 BLOOM); GLYCERIN; FD&C RED NO. 40; TITANIUM DIOXIDE; FD&C BLUE NO. 1

Nestabs One

DESCRIPTION

DESCRIPTION: Nestabs® One is a prescription prenatal multi-vitamin/mineral in the form of a purple, opaque softgel capsule imprinted “ONE” for oral administration.

DOSAGE FORMS AND STRENGTHS

Each NESTABS® ONE Softgel contains:
Vitamin C (as calcium ascorbate) 18 mg
Vitamin D (as cholecalciferol) 6.25 mcg
Vitamin E (as d-alpha tocopheryl acetate) 10 mg
Vitamin B6 (as pyridoxine HCl) 30 mg
Folate (as (6S)-5 1 mg DFE*
-methyltetrahydrofolate -Quatrefolic®) ‡
Vitamin B12 (as cyanocobalamin) 15 mcg
Iron (as carbonyl iron and ferrous 38 mg
bis-glycinate chelate -Ferrochel®) ‡‡
Zinc (as zinc oxide) 20 mg
Magnesium (as magnesium oxide) 15 mg
DHA (Docosahexaenoic Acid from Algal Oil) 225 mg
*Dietary Folate Equivalent (DFE)

INACTIVE INGREDIENT

Other Ingredients: Gelatin capsule (bovine gelatin, glycerin, purified water, titanium dioxide, FD&C Red #40, FD&C Blue #1), soy lecithin, docusate sodium, white beeswax.
Contains Soy.

INDICATIONS AND USAGE

INDICATION AND USAGE: Nestabs® One is a prescription prenatal multi-vitamin/mineral supplement with DHA that can be taken throughout pregnancy and during the postnatal period for both lactating and non-lactating mothers.
Nestabs® One may also be useful in improving the nutritional status of women prior to conception. The usual dose is one softgel daily, or as directed by a physician.

CONTRAINDICATIONS

CONTRAINDICATIONS: This product is contraindicated in patients with a known hypersensitivity to any of the
ingredients.

BOXED WARNING

WARNING: Accidental overdose of iron-containing products is a leading cause of fatal poisoning in children under 6 years of age. KEEP THIS PRODUCT OUT OF THE REACH OF CHILDREN. In case of accidental overdose, call a doctor or poison control center immediately

WARNINGS

WARNINGS: Ingestion of more than 3 grams of omega-3 fatty acids per day has been shown to have potential antithrombotic effects, including increased bleeding time and INR.

Administration of omega-3 fatty acids should be avoided in patients on anticoagulants and in those known to have an inherited or acquired bleeding diathesis.

Folic acid alone is improper therapy in the treatment of pernicious anemia and other megaloblastic anemias where vitamin B12 is deficient.

PRECAUTIONS

PRECAUTIONS: Folic acid in doses above 0.1mg daily may obscure pernicious anemia in that hematologic remission can occur while neurological manifestations remain progressive.

ADVERSE REACTIONS

ADVERSE REACTIONS: Allergic sensitization has been reported following both oral and parenteral administration of folic acid.

DOSAGE AND ADMINISTRATION: One softgel taken orally each day, or as directed by a physician.

STORAGE AND HANDLING

STORAGE: Store between 15-30°C (59°-86°F). Protect from extreme temperatures. Freezing & excessive heat may damage softgels.

HOW SUPPLIED: Nestabs® One softgels for oral
administration are supplied in child resistant bottles
containing 30 softgels, Item 50967-410-30 and as
professional samples, Item 50967-410-03.

Rx

To report a serious adverse event or obtain product information, contact 1-800-664-1490.

Distributed By:
Womens Choice Pharmaceuticals, LLC
Berwyn, PA 19312
www.wcpharma.com

Nestabs® is a registered trademark of
Womens Choice Pharmaceuticals, LLC
‡ Quatrefolic® under exclusive license from
Gnosis, S.p.A covered by U.S. Patent No. 7,947,662
and patents pending PCT/EP2008/052037
and PCT/EP2008/052034
‡‡ Ferrochel® is a registered trademark of
Albion Laboratories, Inc., covered by
U.S. Patents 6,716,814 and 7,838,042.